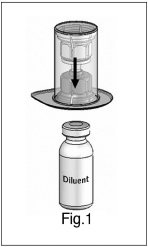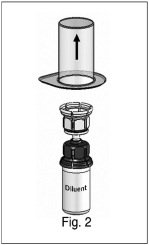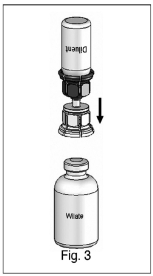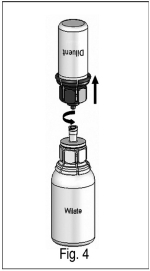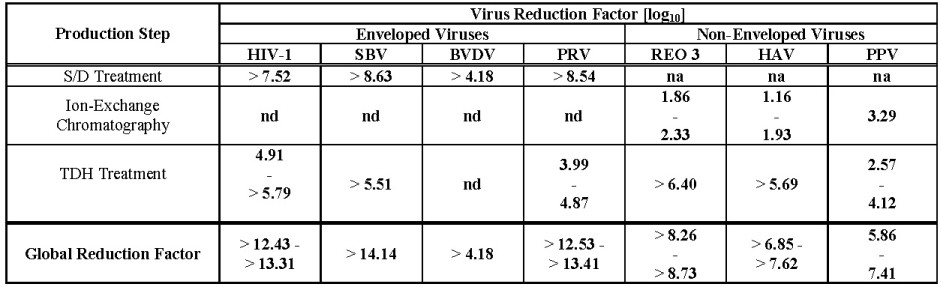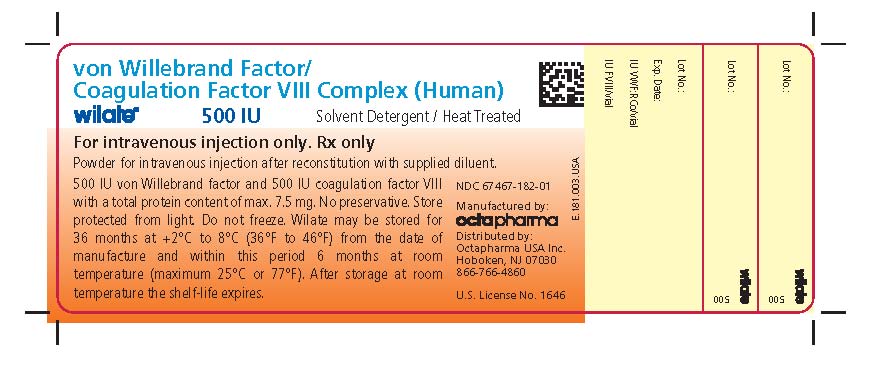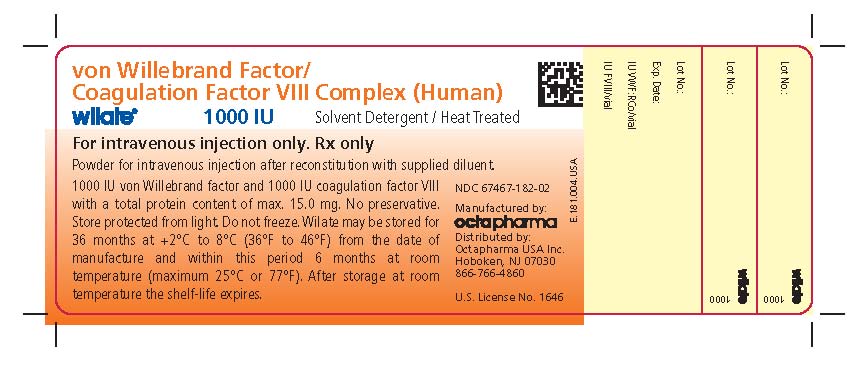 DRUG LABEL: Wilate - von Willebrand Factor/Coagulation Factor VIII Complex (Human)
NDC: 67467-182 | Form: POWDER, FOR SOLUTION
Manufacturer: Octapharma Pharmazeutika Produktionsgesellschaft m.b.H.
Category: other | Type: PLASMA DERIVATIVE
Date: 20100820

ACTIVE INGREDIENTS: ANTIHEMOPHILIC FACTOR HUMAN 100 [iU]/1 mL; VON WILLEBRAND FACTOR HUMAN 100 [iU]/1 mL

HIGHLIGHTS OF PRESCRIBING INFORMATION

These highlights do not include all the information needed to use Wilate safely and effectively. See full prescribing information for Wilate.
Wilate, von Willebrand Factor/Coagulation Factor VIII Complex (Human), Powder for Solution, for Intravenous Use Only.
Initial U.S. Approval: 2009

1 INDICATIONS AND USAGE

Wilate is a von Willebrand Factor/Coagulation Factor VIII Complex (Human) indicated for the treatment of spontaneous and trauma-induced bleeding episodes in patients with severe von Willebrand disease (VWD) as well as patients with mild or moderate VWD in whom the use of desmopressin is known or suspected to be ineffective or contraindicated. (1)

Wilate is not indicated for the prophylaxis of spontaneous bleeding episodes, or the prevention of excessive bleeding during and after surgery in VWD patients.

Wilate is not indicated for Hemophilia A

2 DOSAGE AND ADMINISTRATION

For Intravenous Use Only

Type of Hemorrhages | Loading Dosage (IU VWF:RCo /kg BW) | Maintenance Dosage (IU VWF:RCo /kg BW) | Therapeutic Goal
Minor | 20-40 IU/kg | 20-30 IU/kg every 12-24 hours | VWF:RCo and FVIII activity through levels of >30%
Major | 40-60 IU/kg | 20-40 IU/kg every 12-24 hours | VWF:RCo and FVIII activity through levels of >50%

3 DOSAGE FORMS AND STRENGTHS

Wilate is a sterile, lyophilized powder for reconstitution for intravenous injection, provided in the following nominal strengths per vial (3):

500 IU VWF:RCo and 500 IU FVIII activities in 5 mL

1000 IU VWF:RCo and 1000 IU FVIII activities in 10 mL

4 CONTRAINDICATIONS

Hypersensitivity with known anaphylactic or severe systemic reaction to human plasma-derived products, any ingredient in the formulation, or components of the container. (4)

5 WARNINGS AND PRECAUTIONS

Hypersensitivity reaction (5.1)

Thromboembolic events associated with von Willebrand factor/Coagulation Factor FVIII (VWF/FVIII) products: plasma levels of FVIII activity should be monitored to avoid sustained excessive FVIII levels, which may increase the risk of thrombotic events (5.2)

Potential for inducing antibodies to Factor VIII (inhibitors) and antibodies to VWF, especially in VWD type 3 patients (5.3)

Theoretical risk of infectious agents transmission as the product is made from human plasma (5.4)

6 ADVERSE REACTIONS

The most common adverse reactions in clinical studies on VWD were urticaria and dizziness (each 2.2%) (6.1).

To report SUSPECTED ADVERSE REACTIONS, contact Octapharma USA Inc. at phone # 866-766-4860 or FDA at 1-800-FDA-1088 or www.fda.gov/medwatch.

7 DRUG INTERACTIONS

None known (7).

8 USE IN SPECIFIC POPULATIONS

Pregnancy: No human or animal data. Use only if clearly needed (8.1).

See 17 for PATIENT COUNSELING INFORMATION.

Revised: August 2010

_____________________________________________

FULL PRESCRIBING INFORMATION

1 INDICATIONS AND USAGE

Wilate is a von Willebrand Factor/Coagulation Factor VIII Complex (Human) indicated for the treatment of spontaneous and trauma-induced bleeding episodes in patients with severe von Willebrand disease (VWD) as well as patients with mild or moderate VWD in whom the use of desmopressin is known or suspected to be ineffective or contraindicated.

Clinical trials to evaluate the safety and efficacy of prophylactic dosing with Wilate to prevent spontaneous bleeding have not been conducted in VWD subjects.

Wilate is not indicated for the prevention of excessive bleeding during and after surgery in VWD patients.

Wilate is not indicated for Hemophilia A.

2 DOSAGE AND ADMINISTRATION

- For Intravenous Use after Reconstitution
- Treatment should be initiated under the supervision of a physician experienced in the treatment of coagulation disorders.
- Each vial of Wilate contains the labeled amount in International Units (IU) of von Willebrand factor (VWF) activity as measured with the Ristocetin cofactor assay (VWF:RCo), and coagulation factor VIII (FVIII) activity measured with the chromogenic substrate assay.
- The number of units of VWF:RCo and FVIII activities administered is expressed in IU, which are related to the current WHO standards for VWF and FVIII products. VWF:RCo and FVIII activities in plasma are expressed either as a percentage (relative to normal human plasma) or in IU (relative to the International Standards for VWF:RCo and FVIII activities in plasma).

2.1 Dosage in von Willebrand Disease

The ratio between VWF:RCo and FVIII activities in Wilate is approximately 1:1.

The dosage should be adjusted according to the extent and location of the bleeding. In VWD type 3 patients, especially in those with gastro-intestinal (GI) bleedings, higher doses may be required.

2.2 Dosing Schedule

Physician supervision of the treatment regimen is required. A guide for dosing in the treatment of major and minor hemorrhages is provided in Table 1 .

The careful control of replacement therapy is especially important in life-threatening hemorrhages. When using a FVIII-containing VWF product, the treating physician should be aware that continued treatment may cause an excessive rise in FVIII activity.[ 1 ]

Table 1 Guide to Wilate Dosing for Treatment of Minor and Major Hemorrhages

Type of Hemorrhages | Loading Dosage (IU VWF:RCo /kg BW) | Maintenance Dosage (IU VWF:RCo /kg BW) | Therapeutic Goal
Minor Hemorrhages | 20-40 IU/kg | 20-30 IU/kg every 12-24 hours* | VWF:RCo and FVIII activity through levels of >30%
Major Hemorrhages | 40-60 IU/kg | 20-40 IU/kg every 12-24 hours* | VWF:RCo and FVIII activity through levels of >50%

*This may need to be continued for up to 3 days for minor hemorrhages and 5-7 days for major hemorrhages

Repeat doses are administered for as long as needed based upon repeat monitoring of appropriate clinical and laboratory measures.

Although dose can be estimated by the guidelines above, it is highly recommended that whenever possible, appropriate laboratory tests should be performed on the patient’s plasma at suitable intervals to assure that adequate VWF:RCo and FVIII activity levels have been reached and are maintained.

In the unlikely event that a patient who is actively bleeding should miss a dose, it may be appropriate to adopt a dosage depending on the level of coagulation factors measured, extent of the bleeding, and patient's clinical condition.

2.3 Administration

Wilate is administered via intravenous infusion. Wilate is provided with a Mix2Vial TM transfer device for reconstitution of the freeze-dried powder in diluent, a 10-mL syringe, an infusion set and two alcohol swabs.

Instructions for Reconstitution:

1) Warm the Powder and Diluent in the closed vials up to room temperature. This temperature should be maintained during reconstitution. If a water bath is used for warming, care must be taken to avoid water coming into contact with the rubber stoppers (latex-free) or the caps of the vials. The temperature of the water bath should not exceed +37°C (98°F).

2) Remove the caps from the concentrate (Wilate) vial and the diluent vial and clean the rubber stoppers with an alcohol swab.

3) Peel away the lid of the outer package of the Mix2Vial™ transfer set. To maintain sterility, leave the Mix2Vial™ device in the clear outer packaging. Place the diluent vial on a level surface and hold the vial firmly. Take the Mix2Vial™ in its outer package and invert it over the diluent vial. Push the blue plastic cannula of the Mix2Vial™ firmly through the rubber stopper of the diluent vial (Fig. 1). While holding onto the diluent vial, carefully remove the outer package from the Mix2Vial™, being careful to leave the Mix2Vial™ attached firmly to the diluent vial (Fig. 2).

4) With the concentrate (Wilate) vial held firmly on a level surface, quickly invert the diluent vial with the Mix2Vial™ attached and push the transparent plastic cannula end of the Mix2Vial™ firmly through the stopper of the concentrate (Wilate) vial (Fig. 3). The diluent will be drawn into the concentrate (Wilate) vial by the vacuum.

5) With both vials still attached, gently swirl the product vial to ensure the product is fully dissolved to a clear solution. Once the contents of the Wilate vial are completely dissolved, firmly hold both the transparent and blue parts of the Mix2Vial™. Unscrew the Mix2Vial™ into two separate pieces (Fig. 4) and discard the empty diluent vial and the blue part of the Mix2Vial™.

- The powder should be reconstituted only directly before injection. As Wilate contains no preservatives, the solution should be used immediately after reconstitution.
- Parenteral drug products should be inspected visually for particulate matter and discoloration prior to administration, whenever solution and container permit.
- The filtered solution is clear or slightly opalescent, colourless or slightly yellow. If the concentrate fails to dissolve completely or an aggregate is formed, the preparation must not be used.

Instructions for Injection:

1. With the Wilate vial still upright, attach a plastic disposable syringe to the Mix2Vial™ (transparent plastic part). Invert the system and draw the reconstituted Wilate into the syringe.
2. Once Wilate has been transferred into the syringe, firmly hold the barrel of the syringe (keeping the syringe plunger facing down) and detach the Mix2Vial™ from the syringe. Discard the Mix2Vial™ (transparent plastic part) and empty Wilate vial.
3. Clean the intended injection site with an alcohol swab.
4. Attach a suitable infusion needle to the syringe.
5. Inject the solution intravenously at a slow speed of 2-4 mL/minute.

- As a precautionary measure, the patient’s pulse rate should be measured before and during the injection. If a marked increase in the pulse rate occurs, the injection speed must be reduced or the administration must be interrupted.
- Any unused product or waste material should be disposed of in accordance with local requirements.

Incompatibilities

Wilate must not be mixed with other medicinal products or administered simultaneously with other intravenous preparation in the same infusion set.

3 DOSAGE FORMS AND STRENGTHS

Wilate is a sterile, lyophilized powder for reconstitution for intravenous injection, provided in the following nominal strengths per vial:

- 500 IU VWF:RCo and 500 IU FVIII activities in 5-mL
- 1000 IU VWF:RCo and 1000 IU FVIII activities in 10-mL

4 CONTRAINDICATIONS

Wilate is contraindicated for patients who have known anaphylactic or severe systemic reaction to plasma-derived products, any ingredient in the formulation, or components of the container. For a complete listing of ingredients, see Description (11).

5 WARNINGS AND PRECAUTIONS

5.1 Hypersensitivity

Hypersensitivity or allergic reactions (which may include angioedema, burning and stinging at the infusion site, chills, flushing, generalized urticaria, headache, hives, hypotension, lethargy, nausea, restlessness, tachycardia, tightness of the chest, tingling, vomiting, wheezing) have been observed upon use of Wilate, and may in some cases progress to severe anaphylaxis (including shock) with or without fever.[ 2 ] Closely monitor patients receiving Wilate and carefully observe for any symptoms throughout the infusion period.

Inform patients of the early signs of hypersensitivity reactions including hives, generalized urticaria, tightness of the chest, wheezing, hypotension, and anaphylaxis. If allergic symptoms occur, discontinue the administration immediately and contact the physician. Since inhibitor antibodies may occur concomitantly with anaphylactic reactions, patients experiencing an anaphylactic reaction should also be evaluated for the presence of inhibitors.[ 2 ]

5.2 Thromboembolic Risk

When using a FVIII-containing VWF product, the treating physician should be aware that continued treatment may cause an excessive rise in FVIII activity.[ 1 ] Monitor plasma levels of VWF:RCo and FVIII activities in patients receiving Wilate to avoid sustained excessive VWF and FVIII activity levels, which may increase the risk of thrombotic events.

5.3 Inhibitor Formation

Patients with VWD, especially type 3 patients, may potentially develop neutralizing antibodies (inhibitors) to VWF. If a patient develops inhibitor to VWF (or FVIII), the condition will manifest itself as an inadequate clinical response. Thus, if the expected VWF activity plasma levels are not attained, or if bleeding is not controlled with an adequate dose or repeated dosing, perform an appropriate assay to determine if a VWF inhibitor is present. In patients with antibodies against VWF, VWF is not effective and infusion of this protein may lead to severe adverse events. Consider other therapeutic options for such patients. Physicians with experience in the care of patients with hemostatic disorders should direct their management.[ 3 ] In all such cases, it is recommended that a center specialized in bleeding disorders be contacted.

Since inhibitor antibodies may occur concomitantly with anaphylactic reactions, patients experiencing an anaphylactic reaction should also be evaluated for the presence of inhibitors.[ 2 ]

5.4 Infection Risk from Human Plasma

Wilate is made from human plasma. Because this product is made from human blood, it may carry a risk of transmitting infectious agents, e.g., viruses, and theoretically, the variant Creutzfeldt-Jakob disease (vCJD) agent. There is also the possibility that unknown infectious agents may be present in such products. The risk that such products will transmit viruses has been reduced by screening plasma donors for prior exposure to certain viruses, by testing for the presence of certain current virus infections, and by inactivating and removing certain viruses during manufacture. Despite these measures, such products may still potentially transmit disease. [ 4 ]

Record the batch number of the product every time Wilate is administered to a patient, and consider appropriate vaccination (against hepatitis A and B virus) of patients in regular/repeated receipt of Wilate. ALL infections thought by a physician possibly to have been transmitted by this product should be reported by the physician or other healthcare provider to Octapharma USA, Inc., telephone # 1-866-766-4860.

5.5 Monitoring and Laboratory Tests

Monitor plasma levels of VWF:RCo and FVIII activities in patients receiving Wilate to avoid sustained excessive VWF and FVIII activity levels, which may increase the risk of thrombotic events, particularly in patients with known clinical or laboratory risk factors.

Monitor for development of VWF and FVIII inhibitors. Perform assays to determine if VWF and/or FVIII inhibitor(s) is present if bleeding is not controlled with the expected dose of Wilate. [ 5 ]

6 ADVERSE REACTIONS

The most common adverse reactions to treatment with Wilate in patients with VWD have been urticaria and dizziness.

The most serious adverse reactions to treatment with Wilate in patients with VWD have been hypersensitivity reactions.

6.1 Clinical Trials Experience

Because clinical trials are conducted under widely varying conditions, adverse reaction rates observed in the clinical trials of a drug cannot be directly compared to rates in the clinical trails of another drug and may not reflect the rates observed in clinical practice.

There were 92 VWD patients who received Wilate on 5676 occasions including clinical studies that involved prophylactic use, treatment on demand, surgery, and pharmacokinetics. Their safety data showed that the most common adverse reactions were urticaria and dizziness (each with 2 patients; 2.2%). There were also four patients (4.4%) who showed seroconversion for antibodies to parvovirus B19 not accompanied by clinical signs of disease. Seroconversion has not been reported since implementation of minipool testing of plasma used for the manufacture of Wilate.

6.2 Post-Marketing Experience

The following adverse reactions have been identified during the post approval use of Wilate. Because these reactions are reported voluntarily from a population of uncertain size, it is not always possible to reliably estimate their frequency or establish a causal relationship to product exposure.

Post-marketing adverse reactions reported in patients treated for VWD include hypersensitivity reactions, dyspnea, nausea, vomiting, and cough.

7 DRUG INTERACTIONS

No interactions with other medicinal products are known.

8 USE IN SPECIFIC POPULATIONS

8.1 Pregnancy

Pregnancy Category C. Animal reproduction studies have not been conducted with Wilate. It is also not known whether Wilate can cause fetal harm when administered to a pregnant woman or can affect reproduction capacity. Wilate should be given to a pregnant woman only if clearly needed.

8.2 Labor and Delivery

Wilate has not been studied in labor or delivery. It should be administered to VWF-deficient women at labor or delivery only if clearly indicated. [ 6 ]

8.3 Nursing Mothers

Wilate has not been studied in lactating women.

8.4 Pediatric Use

Eleven pediatric patients with VWD between 5 to 16 years of age (8 type 3, 1 type 2, 2 type 1) were treated with Wilate for 234 bleeding episodes (BEs) in clinical studies. These studies showed that 88% of the BEs were treated successfully in this population (Table 7). No dose adjustment is needed for pediatric patients as administered dosages were similar to those used in the adult population (Table 8).

8.5 Geriatric Use

Although some of the patients who participated in the Wilate studies were over 65 years of age, the number of patients was inadequate to allow subgroup analysis to support recommendations in the geriatric population.

11 DESCRIPTION

Wilate is a human plasma-derived, sterile, purified, double virus inactivated von Willebrand Factor/Coagulation Factor VIII Complex (Human). Wilate is supplied as a lyophilized powder for reconstitution for intravenous injection.

Wilate is labeled with the actual VWF:RCo and FVIII activities in IU per vial. The VWF activity (VWF:RCo) is determined using a manual agglutination method referenced to the current “WHO International Standard for von Willebrand Factor Concentrate”. The FVIII activity is determined using a chromogenic substrate assay referenced to the current “WHO International Standard for Human Coagulation Factor VIII Concentrate”. The assay methodologies are according to European Pharmacopoeia (Ph.Eur.).

Wilate contains no preservative. The diluent for reconstitution of the lyophilized powder is Water for Injection with 0.1% Polysorbate 80.

No albumin is added as a stabilizer. The resulting specific activity of Wilate is ≥ 60 IU VWF:RCo and ≥ 60 IU FVIII activities per mg of total protein.

The nominal composition of Wilate is as follows:

Component | Quantity/ 5 mL vial | Quantity/ 10 mL vial
VWF:RCo | 500 IU | 1000 IU
FVIII | 500 IU | 1000 IU
Total protein | ≤ 7.5 mg | ≤ 15.0 mg
Glycine | 50 mg | 100 mg
Sucrose | 50 mg | 100 mg
Sodium chloride | 117 mg | 234 mg
Sodium citrate | 14.7 mg | 29.4 mg
Calcium chloride | 0.8 mg | 1.5 mg
Water for injection | 5 mL | 10 mL
Polysorbate 80 | 1 mg/mL | 1 mg/mL

Wilate is derived from large pools of human plasma collected in U.S. FDA approved plasma donation centers. All plasma donations are tested for viral markers in compliance with requirements of EU CPMP and FDA guidances. In addition, the limit for the titer of human parvovirus B19 DNA in the manufacturing pool is set not to exceed 10 ^4 IU/mL.

The product is manufactured from cryoprecipitate, which is reconstituted in a buffer and treated with aluminum hydroxide followed by two different chromatography steps, ultra- and diafiltration, and sterile filtration. The manufacturing process includes two virus inactivation steps, namely, treatment with an organic solvent/detergent (S/D) mixture, composed of tri-n-butyl phosphate (TNBP) and Octoxynol-9, and a terminal dry heat (TDH) treatment of the lyophilized product in final container [at +100°C (212°F) for 120 minutes at a specified residual moisture level of 0. 7 – 1.6%]. In addition, the ion-exchange chromatography step utilized during Wilate manufacturing also removes some viruses [ 7 ]. The mean cumulative virus reduction factors of these steps are summarized in Table 2 .

Table 2 Virus Reduction During Wilate Manufacturing

na: not applicable

nd: not done (S/D reagents present)

HIV-1: Human Immunodeficiency Virus - 1

SBV: Sindbis Virus

BVDV: Bovine Viral Diarrhea Virus

PRV: Pseudorabies Virus

REO 3: Reovirus Type 3

HAV: Hepatitis A Virus

PPV: Porcine Parvovirus

12 CLINICAL PHARMACOLOGY

12.1 Mechanism of Action

VWF and FVIII are normal constituents of human plasma. VWF is a multimeric protein with two key functions. It is an adhesive molecule, which mediates the binding between platelets and damaged sub-endothelial tissues. It is also a carrier protein, involved in the transport and stabilization of FVIII. Patients suffering from VWD have a deficiency or abnormality of VWF. This reduction in VWF concentration in the bloodstream result in a correspondingly low FVIII activity and an abnormal platelet function thereby resulting in excessive bleeding. [ 8 ]

The VWF in Wilate is derived from normal human plasma and is expected to behave in the same way as endogenous VWF. Thus, administration of VWF allows correction of the hemostatic abnormalities in VWD patients at two levels:

- The VWF re-establishes platelet adhesion to the vascular sub-endothelium at the site of vascular damage (as it binds both to the vascular sub-endothelium and to the platelet membrane), providing primary hemostasis, as shown by the shortening of the bleeding time. This effect occurs immediately.
- The VWF induces correction of the associated FVIII deficiency in VWD. Administered intravenously, VWF binds endogenous FVIII (which is produced normally by the patient), and by stabilizing this factor, avoids its rapid degradation. This action is slightly delayed. However, administration of a FVIII-containing VWF preparation like Wilate rapidly restores the FVIII activity level to normal.[ 8 ]

12.2 Pharmacodynamics

There have been no specific pharmacodynamic studies on Wilate.

12.3 Pharmacokinetics

An open label, prospective, randomized, controlled, two-arm cross-over Phase 2 study with Wilate and a comparator product was conducted at 6 sites in the US. In this study, pharmacokinetic (PK) profiles of Wilate were determined by FVIII activity, VWF:RCo, VWF:Ag, and VWF:CB.

Each of twenty-two subjects with inherited VWD [Type 1, n=6; Type 2, n=9 (6 Type 2A, 1 Type 2B, and 2 Type 2M); and Type 3, n=7] received an intravenous bolus dose of Wilate containing approximately 40 IU of VWF:RCo/kg BW. Twenty subjects completed the study as per protocol. PK parameters of VWF:RCo and FVIII are summarized in Table 3 and Table 4 , respectively.

Table 3 Pharmacokinetic Parameters of VWF:RCo:mean ± SD (range)

Parameters | VWD type I (n = 5) | VWD type II (n = 9) | VWD type III (n = 6) | Total (n = 20)
Cmax (IU/dL) | 74 ± 13; (62 - 91) | 77 ± 18; (40 - 100) | 79 ± 13; (65 - 102) | 76 ± 15; (40 - 102)
AUC(0-inf); (IU*hr/dL) | 1633 ± 979; (984 - 3363) | 1172 ± 421; (571 - 1897) | 995 ± 292; (527 - 1306) | 1235 ± 637; (527 - 3363)
Half-life (hrs) | 24.7 ± 17.9; (11.2 - 48.5) | 15.3 ± 6.3; (6.0 - 26.4) | 9.1± 2.6; (5.7 - 12.9) | 15.8 ± 11.0; (5.7 - 48.5)
CL (mL/h/kg) | 3.1 ± 1.1; (1.2 - 4.1) | 4.1 ± 1.7; (2.0 - 7.1) | 4.2 ± 1.4; (3.0 - 6.6) | 3.9 ± 1.5; (1.2 - 7.1)
Vss (mL/kg) | 81.7 ± 38.5; (15.3 - 74.2) | 76.6 ± 35.4; (45.3 - 158.8) | 49.4 ± 16.7; (29.7 - 67.1) | 69.7 ± 33.2; (29.7 - 158.8)
MRT (hrs) | 32.7 ± 25.8; (15.3 - 74.2) | 19.7 ± 5.6; (9.9 - 27.1) | 11.9 ± 2.9; (9.2 - 15.9) | 20.6 ± 14.8; (9.2 - 74.2)
Recovery; (%IU/kg) | 1.8 ± 0.2; (1.5 - 2.0) | 1.8 ± 0.5; (1.0 - 2.4) | 2.1 ± 0.3; (1.8 - 2.6) | 1.9 ± 0.4; (1.0 - 2.6)

C max = peak concentration; AUC = area under curve; CL = clearance; Vss = volume of distribution at steady state; MRT = mean residence time

The PK parameters reported in Table 3 are based on VWF:RCo values obtained using a modified Behring Coagulation System (BCS) analytical method. The modified BCS was used because of its validated lower variability compared to the standard BCS. The measured concentrations (IU VWF:RCo/mL) are higher by the modified BCS than by the standard BCS analytical method which is used in some clinical laboratories. Dose adjusted C max and AUC determined by this modified BCS method are approximately 1.5 times higher than those by the standard BCS method. No difference has been found in incremental recovery.

Table 4 Pharmacokinetic Parameters of FVIII:C: mean ± SD (range) - chromogenic

Parameters | VWD type I (n = 5) | VWD type II (n = 8*) | VWD type III (n = 6) | Total (n = 19*)
Cmax (IU/dL) | 117.1 ± 12.1; (103 - 135) | 147.2 ± 32.6; (102 - 206) | 120 ± 23; (91 - 148) | 112 ± 23; (59 - 148)
AUC(0-inf); (IU*hr/dL) | 1187 ± 382; (523 - 1483) | 1778 ± 1430; (544 - 4821) | 2670 ± 854; (1874 - 3655) | 2290 ± 1045; (464 - 4424)
Half-life (hrs) | 17.5 ± 4.9; (10.9 - 23.8) | 23.6 ± 8.3; (12.6 - 34.7) | 16.1 ± 3.1; (11.8 - 20.1) | 19.6 ± 6.9; (10.9 - 34.7)
CL (mL/h/kg) | 4.4 ± 3.7; (2.5 - 11.0) | 2.5 ± 0.9; (1.2 - 3.5) | 2.0 ± 0.6; (1.4 - 2.8) | 2.9 ± 2.1; (1.2 - 11.0)
Vss (mL/kg) | 95.0 ± 53.8; (57.1 - 190.0) | 79.5 ± 23.1; (52.8 - 116.2) | 44.2 ± 10.4; (31.8 - 57.1) | 72.4 ± 36.2; (31.8 - 190.0)
MRT (hrs) | 24.1 ± 5.5(17.2 - 31.5) | 35.1 ± 14.2; (17.5 - 61.6) | 23.0 ± 3.7; (18.0 - 27.7) | 28.4 ± 11.1; (17.2 - 61.6)
Recovery; (%IU/kg) | 1.9 ± 0.5; (1.1 - 2.5) | 2.2 ± 0.4; (1.6 - 2.8) | 2.5 ± 0.5; (2.0 - 3.0) | 2.2 ± 0.5; (1.1 - 3.0)

C max = peak concentration; AUC = area under curve; CL = clearance; Vss = volume of distribution at steady state; MRT = mean residence time

Effect of age and VWD type on the pharmacokinetics of Wilate:

Due to small sample size (in age or VWD type subsets) and high PK variability, it is difficult to conclude if age or type of VWD had any impact on the pharmacokinetics of Wilate.

Effect of gender on the pharmacokinetics of Wilate:

Based on PK data of Wilate from 8 males and 12 females, it appears that the females (4.35 ± 1.54 mL/hr/kg) had higher clearance of VWF:RCo than the males (3.16 ± 1.19 mL/hr/kg). The clinical significance of this finding is not known.

14 CLINICAL STUDIES

Clinical efficacy of Wilate in the control of bleeding in patients with VWD was determined in four prospective clinical studies. This included treatment of 1068 bleeding episodes (BEs). Data were obtained from 70 VWD patients, of which 37 were type 3. BEs are summarized in Table 5 . The treated BEs were analyzed for efficacy using a set of objective criteria in addition to a subjective 4-point hemostatic efficacy scale (excellent, good, moderate and none). In assessing the efficacy using these objective criteria, the treatment of a bleeding episode was classified as a success only if none of the criteria listed below was fulfilled:

- the episode was additionally treated with another VWF-containing product (excluding whole blood),
- the patient received a blood transfusion during the episode,
- follow-up treatment with a daily dosage of Wilate that was equal or more than 50% (≥ 50%) above the initial dose (for bleeding episodes with more than 1 day of treatment),
- treatment duration of more than 4 days (> 4 days) in cases of severe bleeding (other than gastrointestinal),
- treatment duration of more than 3 days (> 3 days) in cases of moderate bleeding (other than gastrointestinal),
- treatment duration of more than 2 days (> 2 days) in cases of minor bleeding (other than gastrointestinal),
- the last efficacy rating of the bleeding episode was 'moderate' or 'none'.

Among the 70 VWD patients administered Wilate in clinical studies (excluding the PK study), 45 of them received on demand treatment for BEs. Using the above objective criteria, corresponding efficacy for each bleeding event was rated as being successful in 84% of the episodes. In these 45 patients with BEs, 93% of the successfully treated BEs occurred in VWD type 3 patients (n=25).

Table 5 Proportion of successful treatments of bleeding episodes with Wilate (n=45)

 |  |  | 95% CI
Episodes* | Successful | % Successes | Lower CL | Upper CL
1068 | 898 | 84.1 | 81.8 | 86.2

The dosing information for the 972 successfully treated “bleeding episodes” (1423 infusions) for regional bleeding is summarized in Table 6 . For the purpose of assigning success/failure to regional bleeding that occurred at the same time, the bleeding at different sites over the same time span would be counted as separate BEs. Thus, the number of these “episodes” would be different from that in the overall evaluation for success/failure of Wilate in the treatment of bleeding episodes in Table 5 .

Table 6 Administered dosages (VWF:RCo in IU/kg) in bleeding episodes* successfully treated with Wilate: Mean ± SD (Range) (n=45)

Location | All Doses considered |  | Initial Dose |  | Subsequent Doses
 | # of infusions | Dose: Mean ± SD (Range) | # of infusions | Dose: Mean ± SD (Range) | # of infusions | Dose: Mean ± SD (Range)
Joints | 801 | 26 ± 12; (7 - 69) | 542 | 28 ± 13; (7 - 69) | 259 | 21 ± 10; (7 - 60)
Epistaxis | 132 | 24 ± 11; (8 - 78) | 91 | 25 ± 10; (13 - 78) | 41 | 22 ± 14; (8 - 77)
GI Tract | 125 | 40 ± 20; (9 - 76) | 64 | 43 ± 19; (9 - 76) | 61 | 36 ± 21; (9 - 76)
Oral | 41 | 26 ± 14; (8 - 80) | 33 | 27 ± 14; (10 - 80) | 8 | 24 ± 18; (8 - 60)
Gynecologic | 87 | 27 ± 14; (9 - 77) | 52 | 28 ± 17; (12 - 77) | 35 | 26 ± 9; (9 - 52)
Other** | 237 | 23 ± 12; (10 - 95) | 189 | 24 ± 12; (12 - 95) | 48 | 20 ± 13; (10 - 95)

**“Other” Includes mostly muscle bleeds, hematuria, ecchymosis, hematoma and other miscellaneous sites of bleeding

The majority of BEs were treated for 1-3 days. In patients with GI bleeds, the duration for product use to control bleeding could be much longer (up to 7 days).

For pediatric patients (≤16 yrs), a summary of the number of BEs treated and corresponding objective efficacy ratings are provided in Table 7 .

Table 7 Efficacy in bleeding episodes in pediatric population (5 to 16 yrs) (n=11) – Proportion of successful treatments of bleeding episodes with Wilate

 |  |  | 95% CI
Episodes* | Successful | % Successes | Lower CL | Upper CL
234 | 205 | 87.6 | 82.7 | 91.5

The dosing information for the 211 successfully treated bleeding episodes (289 infusions) is summarized in Table 8 . Multiple bleeding sites are counted as separate episodes.

Table 8 Administered dosages (VWF:RCo in IU/kg) in bleeding episodes* successfully treated with Wilate in pediatric population (5 to 16 yrs) (n=11): Mean ± SD (Range)

Location | All Doses considered |  | Initial Dose |  | Subsequent Doses
 | # of infusions | Dose: Mean ± SD (Range) | # of infusions | Dose: Mean ± SD (Range) | # of infusions | Dose: Mean ± SD (Range)
Joints | 158 | 30 ± 13; (12 - 69) | 117 | 32 ± 13; (14 - 69) | 41 | 25 ± 9; (12 - 62)
Epistaxis | 30 | 27 ± 14; (12 - 77) | 25 | 25 ± 10; (14 - 52) | 5 | 37 ± 25; (12 - 77)
GI Tract | 1 | 22; (N/A) | 1 | 22 (N/A) | 0 | N/A
Oral | 23 | 25 ± 8; (16 - 52) | 21 | 24 ± 8; (16 - 52) | 2 | 25 ± 13; (16 - 35)
Gynecologic | 58 | 27 ± 13; (12 - 69) | 33 | 27 ± 16; (12 - 69) | 25 | 26 ± 8; (12 - 52)
Other* | 19 | 25 ± 7; (16 - 37) | 14 | 27 ± 7; (19 - 37) | 5 | 19 ± 4; (16 - 26)

**“Other” Includes mostly muscle bleeds, hematuria, ecchymosis, hematoma and other miscellaneous sites of bleeding

15 REFERENCES

1. Mannucci P.M.: Venous thromboembolism in von Willebrand disease. Thromb Haemost 2002;88:378-379
2. Mollison.P.L., Engelfriet C.P., Contreras M.: Some unfavourable effects of transfusion; in Klein H.G., Anstee D.J. (eds): Mollison's Blood Transfusion in Clinical Medicine. Blackwell Publishing, 2005, pp 666-700
3. Mannucci P.M., Federici A.B.: Antibodies to von Willebrand factor in von Willebrand disease; in Aledort L.M. (ed): Inhibitors to Coagulation Factors. New York, Plenum Press, 1995, pp 87-92
4. Y. Kasper, C.K., Kipnis, S.A. Hepatitis and Clotting Factor Concentrates. JAMA1972; 221:510
5. X. Biggs, R. Jaundice and Antibodies Directed Against Factors VIII and IX in Patients Treated for Haemophilia or Christmas Disease in the United Kingdom. Br J Haematol 1974; 26:313-329
6. Azzi A., Morfini M., Mannucci P.M.: The transfusion-associated transmission of parvovirus B19. Transfus.Med.Rev. 1999;13:194-204
7. Stadler M., et al. Characterisation of a novel high-purity, double virus inactivated von Willebrand Factor and Factor VIII concentrate (Wilate). DOI: 10.1016/j.biologicals. Biologicals 2006, 34:281-288 1-8.
8. Mannucci P.M.: Treatment of von Willebrand's disease. New England Journal of Medicine 2004;351:683-694

16 HOW SUPPLIED/STORAGE AND HANDLING

NDC Number | Size | Protein Amount
67467-182-01; 67467-182-02 | 500 IU VWF:RCo and 500 IU FVIII activities in 5 mL; 1000 IU VWF:RCo and 1000 IU FVIII activities in 10 mL | ≤ 7.5 mg; ≤ 15.0 mg

- Wilate is supplied in a package with a single-dose vial of powder and a vial of diluent (Water for Injection with 0.1% Polysorbate 80), together with a Mix2VialTM transfer device, a 10-mL syringe, an infusion set and two alcohol swabs.
- Each vial of Wilate contains the labeled amount of IU of VWF:RCo activity as measured using a manual agglutination method, and IU of FVIII activity measured with a chromogenic substrate assay.
- Components used in the packaging of Wilate contain no latex.

Shelf life

- Store Wilate for up to 36 months at +2°C to +8°C (36°F to 46°F) protected from light from the date of manufacture. Within this period, Wilate may be stored for a period of up to 6 months at room temperature (maximum of +25°C or 77°F). The starting date of room temperature storage should be clearly recorded on the product carton. Once stored at room temperature, the product must not be returned to the refrigerator. The shelf-life then expires after the storage at room temperature, or the expiration date on the product vial, whichever is earliest. Do not freeze.
- Do not use after the expiration date.
- Store in the original container to protect from light.
- Reconstituted the Wilate powder only directly before injection. Use the solution immediately after reconstitution. Use the reconstituted solution on one occasion only, and discard any remaining solution.

17 PATIENT COUNSELING INFORMATION

- Inform patients of the early signs of hypersensitivity reactions including hives, generalized urticaria, tightness of the chest, wheezing, hypotension, and anaphylaxis. If allergic symptoms occur, patients should discontinue the administration immediately and contact their physician [see Warnings and Precautions (5.1)].
- Inform patients that undergoing multiple treatments with Wilate may increase the risk of thrombotic events thereby requiring frequent monitoring of plasma VWF:RCo and FVIII activities. [see Warnings and Precautions (5.2)].
- Inform patients that there is a potential of developing inhibitors to VWF, leading to an inadequate clinical response. Thus, if the expected VWF activity plasma levels are not attained, or if bleeding is not controlled with an adequate dose or repeated dosing, contact the treating physician.[ 2 ] [see Warnings and Precautions (5.3)].
- Inform patients that despite procedures for screening donors and plasma as well as those for inactivation or removal of infectious agents, the possibility of transmitting infective agents with plasma-derived products cannot be totally excluded [see Warnings and Precautions (5.4)].

Manufactured by:

Octapharma Pharmazeutika Produktionsges.m.b.H.

Oberlaaer Strasse 235

A-1100 Vienna, Austria

U.S. License No. 1646

Distributed by:

Octapharma USA Inc.

121 River Street, 12th floor

Hoboken, NJ 07030

PACKAGE LABEL - PRINCIPAL DISPLAY PANEL

von Willebrand Factor/Coagulation Factor VIII Complex (Human)

Octapharma Pharmazeutika Produktionsges.m.b.H

500IU/5mL

NDC 67467-182-01

1000IU/10mL

NDC 67467-182-02